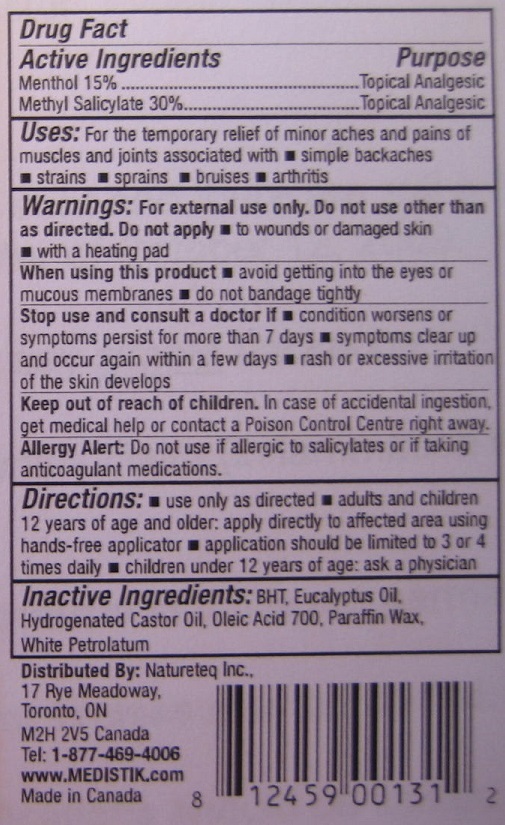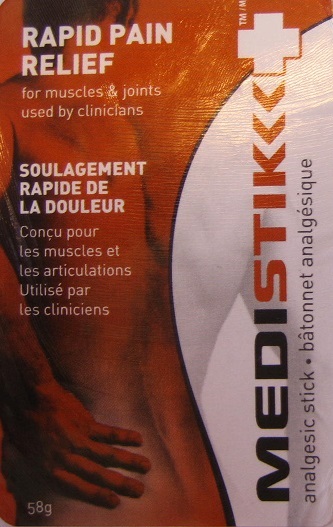 DRUG LABEL: Medistik

NDC: 50231-311 | Form: STICK
Manufacturer: Natureteq Inc.
Category: otc | Type: HUMAN OTC DRUG LABEL
Date: 20240529

ACTIVE INGREDIENTS: MENTHOL 15 g/100 g; METHYL SALICYLATE 30 g/100 g
INACTIVE INGREDIENTS: BUTYLATED HYDROXYTOLUENE; EUCALYPTUS OIL; HYDROGENATED CASTOR OIL; OLEIC ACID; PARAFFIN; PETROLATUM

Natureteq (as PLD) - Medistik (50231-311)

Active Ingredients

Menthol 15%

Methyl Salicylate 30%

Purpose

Topical Analgesic

USES

For the temporary relief of minor aches and pains of muscles and joints associated with

- simple backaches
- strains
- sprains
- bruises
- arthritis

WARNINGS

For external use only. Do not use other than as directed.
Do not apply

- to wounds or damaged skin
- with a heating pad

When using this product

- avoid getting into the eyes or mucous membranes
- do not bandage tightly

Stop use and consult a doctor if

- condition worsens or symptoms persist for more than 7 days
- symptoms clear up and occur again within a few days
- rash or excessive irritation of the skin develops

Keep out of the reach of children. In case of accidental ingestion, get medical help or contact a Poison Control Center right away.
Allergy Alert: Do not use if allergic to salicylates or if taking anticoagulant medications.

Directions

- use only as directed
- adults and children 12 years of age and older: apply directly to the affected area using hands-free applicator
- application should be limited to 3 or 4 times daily
- children under 12 years of age: ask a physician

Inactive Ingredients

BHT, Eucalyptus Oil, Hydrogenated Castor Oil, Oleic Acid 700, Paraffin Wax, White Petrolatum

KEEP OUT OF REACH OF CHILDREN

Enter section text here